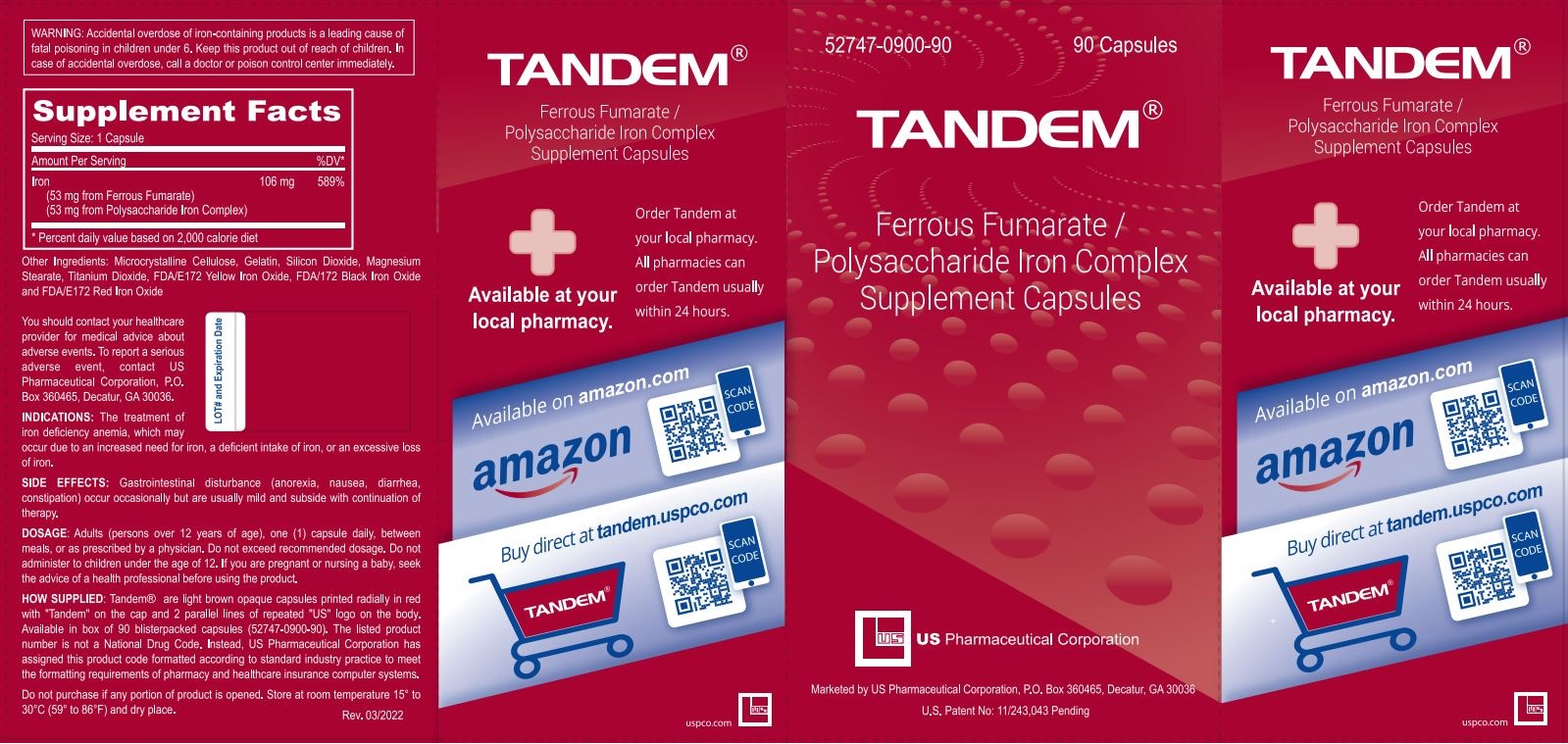 DRUG LABEL: Tandem
NDC: 52747-900 | Form: CAPSULE
Manufacturer: U.S. Pharmaceutical Corporation
Category: other | Type: DIETARY SUPPLEMENT
Date: 20220516

ACTIVE INGREDIENTS: FERROUS FUMARATE 53 mg/1 1; IRON POLYMALTOSE 53 mg/1 1
INACTIVE INGREDIENTS: MICROCRYSTALLINE CELLULOSE 101; GELATIN, UNSPECIFIED; SILICON DIOXIDE; MAGNESIUM STEARATE; TITANIUM DIOXIDE; FERRIC OXIDE YELLOW; FERROSOFERRIC OXIDE; FERRIC OXIDE RED

TANDEM®

STATEMENT OF IDENTITY

Supplement Facts

Serving Size: 1 Capsule

Amount Per Serving

%DV*

Iron

106 mg

589%

(53 mg from Ferrous Fumarate)

(53 mg from Polysaccharide Iron Complex)

* Percent daily value based on 2,000 calorie diet

Other Ingredients: Microcrystalline Cellulose, Gelatin, Silicon Dioxide, Magnesium Stearate, Titanium Dioxide, FDA/E172 Yellow Iron Oxide, FDA/172 Black Iron oxide and FDA/E172 Red Iron Oxide

You should contact your healthcare provider for medical advice about adverse events. To report a serious adverse event, contact US Pharmaceutical Corporation, P.O. Box 360465, Decatur, GA 30036.

INDICATIONS: The treatment of iron deficiency anemia, which may occur due to an increased need for iron, a deficient intake of iron or an excessive loss of iron.

SIDE EFFECTS:

Gastrointestinal disturbance (anorexia, nausea, diarrhea, constipation) occur occasionally but are usually mild and subside with continuation of therapy.

DOSAGE:

Adults (persons over 12 years of age), one (1) capsule daily, between meals, or as prescribed by a physician. Do not exceed recommended dosage. Do not administer to children under the age of 12. If you are pregnant or nursing a baby, seek the advice of a health professional before using the product.

HOW SUPPLIED: Tandem® are light brown opaque capsules printed radially in red with "Tandem" on the cap and 2 parallel lines of repeated "US" logo on the body. Available in box of 90 blister packed capsules (52747-0900-90). The listed product number is not a National Drug Code. Instead, US Pharmaceutical Corporation has assigned this product code formatted according to standard industry practice to meet the formatting requirements of pharmacy and healthcare insurance computer systems.

SAFE HANDLING WARNING

Do not purchase if any portion of product is opened. Store at room temperature 15° to 30°C (59° to 86°F) and dry place.

WARNINGS

WARNING: Accidental overdose of iron-containing products is a leading cause of fatal poisoning in children under 6. Keep this product out of reach of children. In case of accidental overdose, call a doctor or poison control center immediately.

HEALTH CLAIM

Ferrous Fumarate / Polysaccharide Iron Complex Supplement Capsules